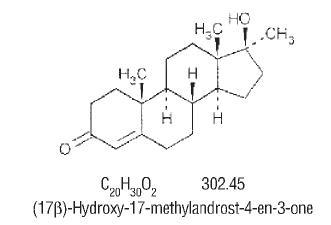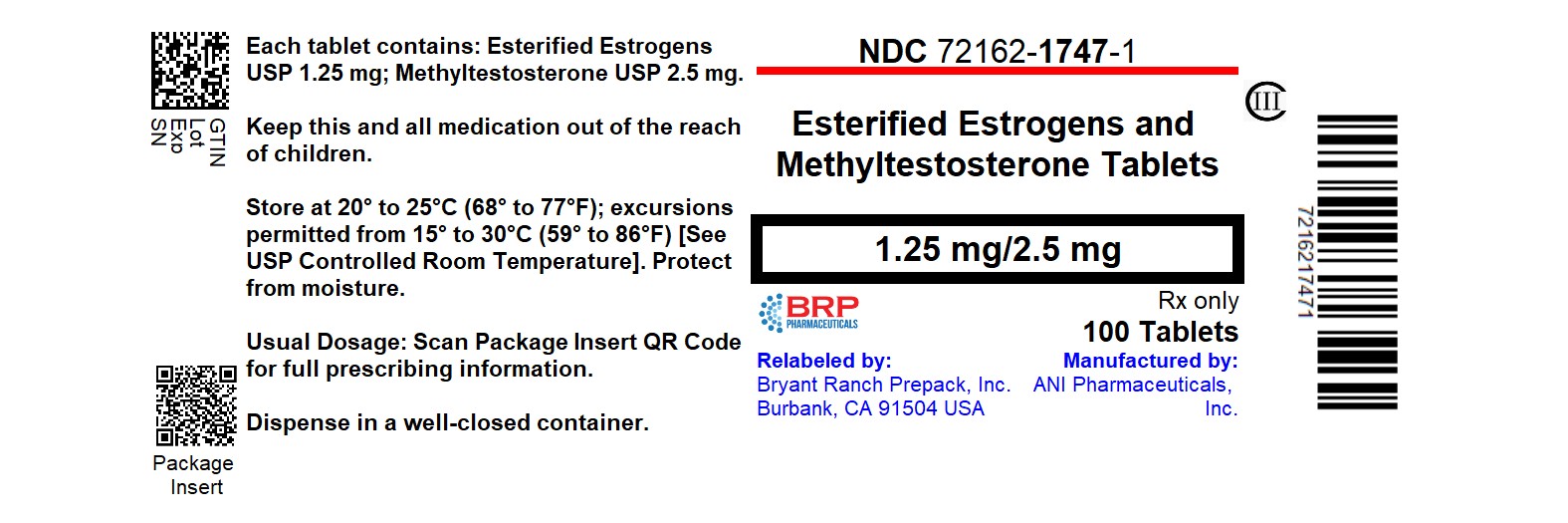 DRUG LABEL: Esterified Estrogens and Methyltestosterone
NDC: 72162-1747 | Form: TABLET
Manufacturer: Bryant Ranch Prepack
Category: prescription | Type: HUMAN PRESCRIPTION DRUG LABEL
Date: 20260226
DEA Schedule: CIII

ACTIVE INGREDIENTS: ESTROGENS, ESTERIFIED 1.25 mg/1 1; METHYLTESTOSTERONE 2.5 mg/1 1
INACTIVE INGREDIENTS: ACACIA; CALCIUM CARBONATE; CARNAUBA WAX; ANHYDROUS CITRIC ACID; SILICON DIOXIDE; DIACETYLATED MONOGLYCERIDES; GELATIN, UNSPECIFIED; ANHYDROUS LACTOSE; MAGNESIUM STEARATE; METHYLPARABEN; MICROCRYSTALLINE CELLULOSE; POVIDONE, UNSPECIFIED; PROPYLENE GLYCOL; PROPYLPARABEN; SHELLAC; SODIUM BENZOATE; SODIUM BICARBONATE; SORBIC ACID; STARCH, CORN; SUCROSE; TALC; TITANIUM DIOXIDE; TROMETHAMINE; FD&C BLUE NO. 1; D&C YELLOW NO. 10; FD&C YELLOW NO. 6

Esterified Estrogens and Methyltestosterone Tablets, 1.25 mg/2.5 mg
Esterified Estrogens and Methyltestosterone Tablets, 0.625 mg/1.25 mg (Half-Strength) CIII

ESTROGENS INCREASE THE RISK OF ENDOMETRIAL CANCER

Close clinical surveillance of all women taking estrogens is important. Adequate diagnostic measures, including endometrial sampling when indicated, should be undertaken to rule out malignancy in all cases of undiagnosed persistent or recurring abnormal vaginal bleeding. There is no evidence that the use of "natural" estrogens results in a different endometrial risk profile than synthetic estrogens at equivalent estrogen doses. (See WARNINGS, Malignant Neoplasms, Endometrial Cancer.)

CARDIOVASCULAR AND OTHER RISKS

Estrogens with or without progestins should not be used for the prevention of cardiovascular disease. (See WARNINGS, Cardiovascular Disorders.)

The Women's Health Initiative (WHI) study reported increased risks of myocardial infarction, stroke, invasive breast cancer, pulmonary emboli, and deep vein thrombosis in postmenopausal women (50 to 79 years of age) during 5 years of treatment with oral conjugated estrogens (CE 0.625 mg) combined with medroxyprogesterone acetate (MPA 2.5 mg) relative to placebo. (See CLINICAL PHARMACOLOGY, Clinical Studies.)

The Women's Health Initiative Memory Study (WHIMS), a substudy of WHI, reported increased risk of developing probable dementia in postmenopausal women 65 years of age or older during 4 years of treatment with oral conjugated estrogens plus medroxyprogesterone acetate relative to placebo. It is unknown whether this finding applies to younger postmenopausal women or to women taking estrogen alone therapy. (See CLINICAL PHARMACOLOGY, Clinical Studies.)

Other doses of oral conjugated estrogens with medroxyprogesterone acetate, and other combinations and dosage forms of estrogens and progestins were not studied in the WHI clinical trials and, in the absence of comparable data, these risks should be assumed to be similar. Because of these risks, estrogens with or without progestins should be prescribed at the lowest effective doses and for the shortest duration consistent with treatment goals and risks for the individual woman.

DESCRIPTION

Esterified Estrogens and Methyltestosterone Tablets: Each dark green, capsule shaped, sugar-coated oral tablet imprinted with “1490” contains: 1.25 mg of Esterified Estrogens, USP and 2.5 mg of Methyltestosterone, USP.

Esterified Estrogens and Methyltestosterone Half-Strength Tablets: Each light green, capsule shaped, sugar-coated oral tablet imprinted with “1507” contains: 0.625 mg of Esterified Estrogens, USP and 1.25 mg of Methyltestosterone, USP.

Esterified Estrogens

Esterified Estrogens, USP is a mixture of the sodium salts of the sulfate esters of the estrogenic substances, principally estrone, that are of the type excreted by pregnant mares. Esterified Estrogens contain not less than 75.0 percent and not more than 85.0 percent of sodium estrone sulfate, and not less than 6.0 percent and not more than 15.0 percent of sodium equilin sulfate, in such proportion that the total of these two components is not less than 90.0 percent.

Methyltestosterone

Methyltestosterone, USP is an androgen. Androgens are derivatives of cyclopentano-perhydrophenanthrene. Endogenous androgens are C-19 steroids with a side chain at C-17, and with two angular methyl groups. Testosterone is the primary endogenous androgen. Fluoxymesterone and methyltestosterone are synthetic derivatives of testosterone.

Methyltestosterone is a white to light yellow crystalline substance that is virtually insoluble in water but soluble in organic solvents. It is stable in air but decomposes in light.

Methyltestosterone structural formula:

Esterified Estrogens and Methyltestosterone Full and Half-Strength Tablets contain the following inactive ingredients: acacia, calcium carbonate, carnauba wax, citric acid, colloidal silicon dioxide, di-acetylated monoglycerides, gelatin, lactose, magnesium stearate, methylparaben, microcrystalline cellulose, pharmaceutical glaze, povidone, propylene glycol, propylparaben, shellac glaze, sodium benzoate, sodium bicarbonate, sorbic acid, starch, sucrose, talc, titanium dioxide, tromethamol, FD&C Blue No. 1 Aluminum Lake, and D&C Yellow No. 10 Aluminum Lake.

Esterified Estrogens and Methyltestosterone Tablets also contain: FD&C Yellow No. 6 Aluminum Lake.

Esterified Estrogens and Methyltestosterone Half-Strength Tablets also contain: FD&C Blue No. 2 Aluminum Lake and Iron Oxide Black.

CLINICAL PHARMACOLOGY

Estrogens:

Endogenous estrogens are largely responsible for the development and maintenance of the female reproductive system and secondary sexual characteristics. Although circulating estrogens exist in a dynamic equilibrium of metabolic interconversions, estradiol is the principal intracellular human estrogen and is substantially more potent than its metabolites, estrone and estriol at the receptor level.

The primary source of estrogen in normally cycling adult women is the ovarian follicle, which secretes 70 to 500 mcg of estradiol daily, depending on the phase of the menstrual cycle. After menopause, most endogenous estrogen is produced by conversion of androstenedione, secreted by the adrenal cortex, to estrone by peripheral tissues. Thus, estrone and the sulfate conjugated form, estrone sulfate, are the most abundant circulating estrogens in postmenopausal women.

Estrogens act through binding to nuclear receptors in estrogen-responsive tissues. To date, two estrogen receptors have been identified. These vary in proportion from tissue to tissue.

Circulating estrogens modulate the pituitary secretion of the gonadotropins, luteinizing hormone (LH) and follicle stimulating hormone (FSH), through a negative feedback mechanism. Estrogens act to reduce the elevated levels of these hormones seen in postmenopausal women.

Estrogen Pharmacokinetics

Distribution
The distribution of exogenous estrogens is similar to that of endogenous estrogens. Estrogens are widely distributed in the body and are generally found in higher concentrations in the sex hormone target organs. Estrogens circulate in the blood largely bound to sex hormone binding globulin (SHBG) and albumin.

Metabolism
Exogenous estrogens are metabolized in the same manner as endogenous estrogens. Circulating estrogens exist in a dynamic equilibrium of metabolic interconversions. These transformations take place mainly in the liver. Estradiol is converted reversibly to estrone, and both can be converted to estriol, which is the major urinary metabolite. Estrogens also undergo enterohepatic recirculation via sulfate and glucuronide conjugation in the liver, biliary secretion of conjugates into the intestine, and hydrolysis in the gut followed by reabsorption. In postmenopausal women, a significant proportion of the circulating estrogens exist as sulfate conjugates, especially estrone sulfate, which serves as a circulating reservoir for the formation of more active estrogens.

Excretion
Estradiol, estrone, and estriol are excreted in the urine along with glucuronide and sulfate conjugates.

Drug Interactions
In vitroand in vivostudies have shown that estrogens are metabolized partially by cytochrome P450 3A4 (CYP3A4). Therefore, inducers or inhibitors of CYP3A4 may affect estrogen drug metabolism. Inducers of CYP3A4 such as St. John’s Wort preparations (Hypericum perforatum), phenobarbital, carbamazepine, and rifampin may reduce plasma concentrations of estrogens, possibly resulting in a decrease in therapeutic effects and/or changes in the uterine bleeding profile. Inhibitors of CYP3A4 such as erythromycin, clarithromycin, ketoconazole, itraconazole, ritonavir and grapefruit juice may increase plasma concentrations of estrogens and may result in side effects.

Clinical Studies

Women’s Health Initiative Studies
The Women’s Health Initiative (WHI) enrolled a total of 27,000 predominantly healthy postmenopausal women to assess the risks and benefits of either the use of oral 0.625 mg conjugated estrogens (CE) per day alone or the use of oral 0.625 mg conjugated estrogens plus 2.5 mg medroxyprogesterone acetate (MPA) per day compared to placebo in the prevention of certain chronic diseases. The primary endpoint was the incidence of coronary heart disease (CHD) (nonfatal myocardial infarction and CHD death), with invasive breast cancer as the primary adverse outcome studied. A “global index” included the earliest occurrence of CHD, invasive breast cancer, stroke, pulmonary embolism (PE), endometrial cancer, colorectal cancer, hip fracture, or death due to other cause. The study did not evaluate the effects of CE or CE/MPA on menopausal symptoms.

The CE-only substudy has concluded. The impact of those results are under review. The CE/MPA substudy was stopped early because, according to the predefined stopping rule, the increased risk of breast cancer and cardiovascular events exceeded the specified benefits included in the "global index." Results of the CE/MPA substudy, which included 16,608 women (average age of 63 years, range 50 to 79; 83.9% White, 6.5% Black, 5.5% Hispanic), after an average follow-up of 5.2 years are presented in Table 1 below.

TABLE 1 Relative and Absolute Risk Seen in the CE/MPA Substudy of WHIa
Eventc | Relative Risk CE/MPA versus Placebo at 5.2 Years (95% CI*) | Placebo n = 8102 | CE/MPA n = 8506
Eventc | Relative Risk CE/MPA versus Placebo at 5.2 Years (95% CI*) | Absolute Risk per 10,000 Women-years
CHD events | 1.29 (1.02 – 1.63) | 30 | 37
Non-fatalMI | 1.32 (1.02 – 1.72) | 23 | 30
CHD death | 1.18 (0.70 – 1.97) | 6 | 7
Invasive breast cancerb | 1.26 (1.00 – 1.59) | 30 | 38
Stroke | 1.41 (1.07 – 1.85) | 21 | 29
Pulmonary embolism | 2.13 (1.39 – 3.25) | 8 | 16
Colorectal cancer | 0.63 (0.43 – 0.92) | 16 | 10
Endometrial cancer | 0.83 (0.47 – 1.47) | 6 | 5
Hip fracture | 0.66 (0.45 – 0.98) | 15 | 10
Death due to causes other than the events above | 0.92 (0.74 – 1.14) | 40 | 37
Global Indexc | 1.15 (1.03 – 1.28) | 151 | 170
Deep vein thrombosisd | 2.07 (1.49 – 2.87) | 13 | 26
Vetebral fracturesd | 0.66 (0.44 – 0.98) | 15 | 9
Other osteoporotic fracturesd | 0.77 (0.69 – 0.86) | 170 | 131
aadapted from JAMA, 2002; 288:321-333
bincludes metastatic and non-metastatic breast cancer with the exception of in situbreast cancer
ca subset of the events was combined in a “global index,” defined as the earliest occurrence of CHD events, invasive breast cancer, stroke, pulmonary embolism, endometrial cancer, colorectal cancer, hip fracture, or death due to other causes
dnot included in the Global Index
*nominal confidence intervals unadjusted for multiple looks and multiple comparisons

For those outcomes included in the "global index," the absolute excess risks per 10,000 women-years in the group treated with CE/MPA were 7 more CHD events, 8 more strokes, 8 more PEs, and 8 more invasive breast cancers, while the absolute risk reductions per 10,000 women-years were 6 fewer colorectal cancers and 5 fewer hip fractures. The absolute excess risk of events included in the "global index" was 19 per 10,000 women-years. There was no difference between the groups in terms of all-cause mortality. (See BOXED WARNINGS, WARNINGS, and PRECAUTIONS.)

Women’s Health Initiative Memory Study
The Women's Health Initiative Memory Study (WHIMS), a substudy of WHI, enrolled 4,532 predominantly healthy postmenopausal women 65 years of age and older (47% were age 65 to 69 years, 35% were 70 to 74 years, and 18% were 75 years of age and older) to evaluate the effects of CE/MPA (0.625 mg conjugated estrogens plus 2.5 mg medroxyprogesterone acetate) on the incidence of probable dementia (primary outcome) compared with placebo.

After an average follow-up of 4 years, 40 women in the estrogen/progestin group (45 per 10,000 women-years) and 21 in the placebo group (22 per 10,000 women-years) were diagnosed with probable dementia. The relative risk of probable dementia in the hormone therapy group was 2.05 (95% CI, 1.21 to 3.48) compared to placebo. Differences between groups became apparent in the first year of treatment. It is unknown whether these findings apply to younger postmenopausal women. (See BOXED WARNINGSand WARNINGS, Dementia.)

Androgens:

Endogenous androgens are responsible for the normal growth and development of the male sex organs and for maintenance of secondary sex characteristics. These effects include the growth and maturation of prostate, seminal vesicles, penis, and scrotum; the development of male hair distribution, such as beard, pubic, chest, and axillary hair, laryngeal enlargement, vocal cord thickening, alterations in body musculature, and fat distribution. Drugs in this class also cause retention of nitrogen, sodium, potassium, phosphorus, and decreased urinary excretion of calcium. Androgens have been reported to increase protein anabolism and decrease protein catabolism. Nitrogen balance is improved only when there is sufficient intake of calories and protein. Androgens are responsible for the growth spurt of adolescence and for the eventual termination of linear growth which is brought about by fusion of the epiphyseal growth centers. In children, exogenous androgens accelerate linear growth rates, but may cause a disproportionate advancement in bone maturation. Use over long periods may result in fusion of the epiphyseal growth centers and termination of growth process. Androgens have been reported to stimulate the production of red blood cells by enhancing the production of erythropoietic stimulating factor.

Androgen Pharmacokinetics
Testosterone given orally is metabolized by the gut and 44 percent is cleared by the liver in the first pass. Oral doses as high as 400 mg per day are needed to achieve clinically effective blood levels for full replacement therapy. The synthetic androgens (methyltestosterone and fluoxymesterone) are less extensively metabolized by the liver and have longer half-lives. They are more suitable than testosterone for oral administration.

Testosterone in plasma is 98 percent bound to a specific testosterone-estradiol binding globulin, and about 2 percent is free. Generally, the amount of this sex-hormone binding globulin in the plasma will determine the distribution of testosterone between free and bound forms, and the free testosterone concentration will determine its half-life.

About 90 percent of a dose of testosterone is excreted in the urine as glucuronic and sulfuric acid conjugates of testosterone and its metabolites; about 6 percent of a dose is excreted in the feces, mostly in the unconjugated form. Inactivation of testosterone occurs primarily in the liver. Testosterone is metabolized to various 17-keto steroids through two different pathways. There are considerable variations of the half-life of testosterone as reported in the literature, ranging from 10 to 100 minutes.

In many tissues the activity of testosterone appears to depend on reduction to dihydrotestosterone, which binds to cytosol receptor proteins. The steroid-receptor complex is transported to the nucleus where it initiates transcription events and cellular changes related to androgen action.

INDICATIONS AND USAGE

Esterified Estrogens and Methyltestosterone Full and Half-Strength Tablets are indicated in the:

- Treatment of moderate to severe vasomotor symptoms associated with the menopause in those patients not improved by estrogens alone. (There is no evidence that estrogens are effective for nervous symptoms or depression without associated vasomotor symptoms, and they should not be used to treat such conditions.)
- Esterified Estrogens and Methyltestosterone Full and Half-Strength Tablets have not been shown to be effective for any purpose during pregnancy and its use may cause severe harm to the fetus.

CONTRAINDICATIONS

Esterified Estrogens and Methyltestosterone Full and Half-Strength Tablets should not be used in women with any of the following conditions:

1. Undiagnosed abnormal genital bleeding.
2. Known, suspected, or history of cancer of the breast.
3. Known or suspected estrogen-dependent neoplasia.
4. Active deep vein thrombosis, pulmonary embolism or history of these conditions.
5. Active or recent (e.g., within the past year) arterial thromboembolic disease (e.g., stroke, myocardial infarction).
6. Liver dysfunction or disease.
7. Esterified Estrogens and Methyltestosterone Full and Half-Strength Tablets should not be used in patients with known hypersensitivity to its ingredients.
8. Known or suspected pregnancy. There is no indication for Esterified Estrogens and Methyltestosterone Full and Half-Strength Tablets in pregnancy. There appears to be little or no increased risk of birth defects in children born to women who have used estrogens and progestins from oral contraceptives inadvertently during early pregnancy. (See PRECAUTIONS.)

Methyltestosterone should not be used in:

1. The presence of severe liver damage.
2. Pregnancy and in breast-feeding mothers because of the possibility of masculinization of the female fetus or breast-fed infant.

WARNINGS

See BOXED WARNINGS.

Warnings Associated with Estrogens

Cardiovascular Disorders

Estrogen and estrogen/progestin therapy has been associated with an increased risk of cardiovascular events such as myocardial infarction and stroke, as well as venous thrombosis and pulmonary embolism (venous thromboembolism or VTE). Should any of these occur or be suspected, estrogens should be discontinued immediately.

Risk factors for arterial vascular disease (e.g., hypertension, diabetes mellitus, tobacco use, hypercholesterolemia, and obesity) and/or venous thromboembolism (e.g., personal history or family history of VTE, obesity, and systemic lupus erythematosus) should be managed appropriately.

Coronary Heart Disease and Stroke:In the Women's Health Initiative (WHI) study, an increase in the number of myocardial infarctions and strokes was observed in women receiving CE compared to placebo. The CE-only substudy has concluded. The impact of those results are under review. (See CLINICAL PHARMACOLOGY, Clinical Studies.)

In the CE/MPA substudy of WHI, an increased risk of coronary heart disease (CHD) events (defined as nonfatal myocardial infarction and CHD death) was observed in women receiving CE/MPA compared to women receiving placebo (37 versus 30 per 10,000 women-years). The increase in risk was observed in year 1 and persisted.

In the same substudy of WHI, an increased risk of stroke was observed in women receiving CE/MPA compared to women receiving placebo (29 versus 21 per 10,000 women-years). The increase in risk was observed after the first year and persisted.

In postmenopausal women with documented heart disease (n = 2,763, average age 66.7 years) a controlled clinical trial of secondary prevention of cardiovascular disease (Heart and Estrogen/Progestin Replacement Study; HERS) treatment with CE/MPA (0.625 mg/2.5 mg per day) demonstrated no cardiovascular benefit. During an average follow-up of 4.1 years, treatment with CE/MPA did not reduce the overall rate of CHD events in postmenopausal women with established coronary heart disease. There were more CHD events in the CE/MPA-treated group than in the placebo group in year 1, but not during the subsequent years. Two thousand three hundred and twenty one women from the original HERS trial agreed to participate in an open-label extension of HERS, HERS II. Average follow-up in HERS II was an additional 2.7 years, for a total of 6.8 years overall. Rates of CHD events were comparable among women in the CE/MPA group and the placebo group in HERS, HERS II, and overall.

Large doses of estrogen (5 mg conjugated estrogens per day), comparable to those used to treat cancer of the prostate and breast, have been shown in a large prospective clinical trial in men to increase the risks of nonfatal myocardial infarction, pulmonary embolism, and thrombophlebitis.

Venous Thromboembolism (VTE.): In the Women's Health Initiative (WHI) study, an increase in VTE was observed in women receiving CE compared to placebo. The CE-only substudy has concluded. The impact of those results are under review. (See CLINICAL PHARMACOLOGY, Clinical Studies.)

In the CE/MPA substudy of WHI, a 2-fold greater rate of VTE, including deep venous thrombosis and pulmonary embolism, was observed in women receiving CE/MPA compared to women receiving placebo. The rate of VTE was 34 per 10,000 women-years in the CE/MPA group compared to 16 per 10,000 women-years in the placebo group. The increase in VTE risk was observed during the first year and persisted.

If feasible, estrogens should be discontinued at least 4 to 6 weeks before surgery of the type associated with an increased risk of thromboembolism, or during periods of prolonged immobilization.

Malignant Neoplasms

Endometrial Cancer:The use of unopposed estrogens in women with intact uteri has been associated with an increased risk of endometrial cancer. The reported endometrial cancer risk among unopposed estrogen users is about 2- to 12-fold greater than in non-users, and appears dependent on duration of treatment and on estrogen dose. Most studies show no significant increased risk associated with use of estrogens for less than one year. The greatest risk appears associated with prolonged use, with increased risks of 15- to 24-fold for 5 to 10 years or more and this risk has been shown to persist for at least 8 to 15 years after estrogen therapy is discontinued.

Clinical surveillance of all women taking estrogen/progestin combinations is important. Adequate diagnostic measures, including endometrial sampling when indicated, should be undertaken to rule out malignancy in all cases of undiagnosed persistent or recurring abnormal vaginal bleeding. There is no evidence that the use of natural estrogens results in a different endometrial risk profile than synthetic estrogens of equivalent estrogen dose. Adding a progestin to estrogen therapy has been shown to reduce the risk of endometrial hyperplasia, which may be a precursor to endometrial cancer.

Breast Cancer:The use of estrogens and progestins by postmenopausal women has been reported to increase the risk of breast cancer. The most important randomized clinical trial providing information about this issue is the Women's Health Initiative (WHI) substudy of CE/MPA. (See CLINICAL PHARMACOLOGY, Clinical Studies.) The results from observational studies are generally consistent with those of the WHI clinical trial and report no significant variation in the risk of breast cancer among different estrogens or progestins, doses, or routes of administration.

The CE/MPA substudy of WHI reported an increased risk of breast cancer in women who took CE/MPA for a mean follow-up of 5.6 years. Observational studies have also reported an increased risk for estrogen/progestin combination therapy, and a smaller increased risk for estrogen alone therapy, after several years of use. In the WHI trial and from observational studies, the excess risk increased with duration of use. From observational studies, the risk appeared to return to baseline in about five years after stopping treatment. In addition, observational studies suggest that the risk of breast cancer was greater, and became apparent earlier, with estrogen/progestin combination therapy as compared to estrogen alone therapy.

In the CE/MPA substudy, 26% of the women reported prior use of estrogen alone and/or estrogen/progestin combination hormone therapy. After a mean follow-up of 5.6 years during the clinical trial, the overall relative risk of invasive breast cancer was 1.24 (95% confidence interval 1.01-1.54), and the overall absolute risk was 41 versus 33 cases per 10,000 women-years, for CE/MPA compared with placebo. Among women who reported prior use of hormone therapy, the relative risk of invasive breast cancer was 1.86, and the absolute risk was 46 versus 25 cases per 10,000 women-years, for CE/MPA compared with placebo. Among women who reported no prior use of hormone therapy, the relative risk of invasive breast cancer was 1.09, and the absolute risk was 40 versus 36 cases per 10,000 women-years for CE/MPA compared with placebo. In the same substudy, invasive breast cancers were larger and diagnosed at a more advanced stage in the CE/MPA group compared with the placebo group. Metastatic disease was rare with no apparent difference between the two groups. Other prognostic factors such as histologic subtype, grade and hormone receptor status did not differ between the groups.

The use of estrogen plus progestin has been reported to result in an increase in abnormal mammograms requiring further evaluation. All women should receive yearly breast examinations by a healthcare provider and perform monthly breast self-examinations. In addition, mammography examinations should be scheduled based on patient age, risk factors, and prior mammogram results.

Dementia

In the Women's Health Initiative Memory Study (WHIMS), 4,532 generally healthy postmenopausal women 65 years of age and older were studied, of whom 35% were 70 to 74 years of age and 18% were 75 or older. After an average follow-up of 4 years, 40 women being treated with CE/MPA (1.8%, n = 2,229) and 21 women in the placebo group (0.9%, n = 2,303) received diagnoses of probable dementia. The relative risk for CE/MPA versus placebo was 2.05 (95% confidence interval 1.21 – 3.48), and was similar for women with and without histories of menopausal hormone use before WHIMS. The absolute risk of probable dementia for CE/MPA versus placebo was 45 versus 22 cases per 10,000 women-years, and the absolute excess risk for CE/MPA was 23 cases per 10,000 women-years. It is unknown whether these findings apply to younger postmenopausal women. (See CLINICAL PHARMACOLOGY, Clinical Studiesand PRECAUTIONS, Geriatric Use.)

The estrogen alone substudy of the Women's Health Initiative Memory Study has concluded. It is unknown whether these findings apply to estrogen alone.

Gallbladder Disease

A 2- to 4-fold increase in the risk of gallbladder disease requiring surgery in postmenopausal women receiving estrogens has been reported.

Glucose Tolerance

A worsening of glucose tolerance has been observed in a significant percentage of patients on estrogen-containing oral contraceptives. For this reason, diabetic patients should be carefully observed while receiving estrogens.

Hypercalcemia

Estrogen administration may lead to severe hypercalcemia in patients with breast cancer and bone metastases. If hypercalcemia occurs, use of the drug should be stopped and appropriate measures taken to reduce the serum calcium level.

Visual Abnormalities

Retinal vascular thrombosis has been reported in patients receiving estrogens. Discontinue medication pending examination if there is sudden partial or complete loss of vision, or a sudden onset of proptosis, diplopia, or migraine. If examination reveals papilledema or retinal vascular lesions, estrogens should be permanently discontinued.

Warnings Associated with Methyltestosterone

In patients with breast cancer, androgen therapy may cause hypercalcemia by stimulating osteolysis. In this case the drug should be discontinued.

Prolonged use of high doses of androgens has been associated with the development of peliosis hepatis and hepatic neoplasms including hepatocellular carcinoma. (See PRECAUTIONS – Carcinogenesis (Androgens)) Peliosis hepatis can be a life-threatening or fatal complication.

Cholestatic hepatitis and jaundice occur with 17-alpha-alkylandrogens at a relatively low dose. If cholestatic hepatitis with jaundice appears or if liver function tests become abnormal, the androgen should be discontinued and the etiology should be determined. Drug-induced jaundice is reversible when the medication is discontinued.

Edema with or without heart failure may be a serious complication in patients with preexisting cardiac, renal, or hepatic disease. In addition to discontinuation of the drug, diuretic therapy may be required.

PRECAUTIONS

General Precautions Associated with Estrogens

Addition of a progestin when a woman has not had a hysterectomy: Studies of the addition of a progestin for 10 or more days of a cycle of estrogen administration, or daily with estrogen in a continuous regimen, have reported a lowered incidence of endometrial hyperplasia than would be induced by estrogen treatment alone. Endometrial hyperplasia may be a precursor to endometrial cancer.

There are, however, possible risks that may be associated with the use of progestins with estrogens compared to estrogen-alone regimens. These include a possible increased risk of breast cancer.

Elevated blood pressure:In a small number of case reports, substantial increases in blood pressure have been attributed to idiosyncratic reactions to estrogens. In a large, randomized, placebo-controlled clinical trial, a generalized effect of estrogens on blood pressure was not seen. Blood pressure should be monitored at regular intervals with estrogen use.

Hypertriglyceridemia:In patients with pre-existing hypertriglyceridemia, estrogen therapy may be associated with elevations of plasma triglycerides leading to pancreatitis and other complications.

Impaired liver function and past history of cholestatic jaundice:Estrogens may be poorly metabolized in patients with impaired liver function. For patients with a history of cholestatic jaundice associated with past estrogen use or with pregnancy, caution should be exercised and in the case of recurrence, medication should be discontinued.

Hypothyroidism:Estrogen administration leads to increased thyroid-binding globulin (TBG) levels. Patients with normal thyroid function can compensate for the increased TBG by making more thyroid hormone, thus maintaining free T4 and T3 serum concentrations in the normal range. Patients dependent on thyroid hormone replacement therapy who are also receiving estrogens may require increased doses of their thyroid replacement therapy. These patients should have their thyroid function monitored in order to maintain their free thyroid hormone levels in an acceptable range.

Fluid retention:Because estrogens may cause some degree of fluid retention, patients with conditions that might be influenced by this factor, such as a cardiac or renal dysfunction, warrant careful observation when estrogens are prescribed.

Hypocalcemia:Estrogens should be used with caution in individuals with severe hypocalcemia.

Ovarian cancer:The CE/MPA substudy of WHI reported that estrogen plus progestin increased the risk of ovarian cancer. After an average follow-up of 5.6 years, the relative risk for ovarian cancer for CE/MPA versus placebo was 1.58 (95% confidence interval 0.77 – 3.24) but was not statistically significant. The absolute risk for CE/MPA versus placebo was 4.2 versus 2.7 cases per 10,000 women-years. In some epidemiologic studies, the use of estrogen alone, in particular for 10 or more years, has been associated with an increased risk of ovarian cancer. Other epidemiologic studies have not found these associations.

Exacerbation of endometriosis:Endometriosis may be exacerbated with administration of estrogens. A few cases of malignant transformation of residual endometrial implants have been reported in women treated post-hysterectomy with estrogen alone therapy. For patients known to have residual endometriosis post-hysterectomy, the addition of progestin should be considered.

Exacerbation of other conditions: Estrogens may cause an exacerbation of asthma, diabetes mellitus, epilepsy, migraine or porphyria, systemic lupus erythematosus, and hepatic hemangiomas and should be used with caution in women with these conditions.

General Precautions Associated with Methyltestosterone

1. Women should be observed for signs of virilization (deepening of the voice, hirsutism, acne, clitoromegaly, and menstrual irregularities). Discontinuation of drug therapy at the time of evidence of mild virilism is necessary to prevent irreversible virilization. Such virilization is usual following androgen use at high doses.
2. Prolonged dosage of androgen may result in sodium and fluid retention. This may present a problem, especially in patients with compromised cardiac reserve or renal disease.
3. Hypersensitivity may occur rarely.
4. Protein-bound iodine (PBI) may be decreased in patients taking androgens.
5. Hypercalcemia may occur. If this does occur, the drug should be discontinued.

Patient Information (Estrogens)

Physicians are advised to discuss the PATIENT INFORMATION leaflet with patients for whom they prescribe Esterified Estrogens and Methyltestosterone Full and Half-Strength Tablets.

Patient Information (Androgens)

The physician should instruct patients to report any of the following side effects of androgens:
Women:Hoarseness, acne, changes in menstrual periods, or more hair on the face.
All Patients:Any nausea, vomiting, changes in skin color or ankle swelling.

Laboratory Tests (Estrogens)

Estrogen administration should be initiated at the lowest dose approved for the indication and then guided by clinical response rather than by serum hormone levels (e.g., estradiol, FSH).

Laboratory Tests (Androgens)

1. Women with disseminated breast carcinoma should have frequent determination of urine and serum calcium levels during the course of androgen therapy. (See WARNINGS.)
2. Because of the hepatotoxicity associated with the use of 17-alpha-alkylated androgens, liver function tests should be obtained periodically.
3. Hemoglobin and hematocrit should be checked periodically for polycythemia in patients who are receiving high doses of androgens.

Drug/Laboratory Test Interactions (Estrogens)

1. Accelerated prothrombin time, partial thromboplastin time, and platelet aggregation time; increased platelet count; increased factors II, VII antigen, VIII antigen, VIII coagulant activity, IX, X, XII, VII-X complex, II-VII-X complex, and beta-thromboglobulin; decreased levels of antifactor Xa and antithrombin III, decreased antithrombin III activity; increased levels of fibrinogen and fibrinogen activity; increased plasminogen antigen and activity.
2. Increased thyroid-binding globulin (TBG) levels leading to increased circulating total thyroid hormone levels as measured by protein-bound iodine (PBI), T4 levels (by column or by radioimmunoassay) or T3 levels by radioimmunoassay. T3 resin uptake is decreased, reflecting the elevated TBG. Free T4 and free T3 concentrations are unaltered. Patients on thyroid replacement therapy may require higher doses of thyroid hormone.
3. Other binding proteins may be elevated in serum (i.e., corticosteroid binding globulin (CBG), sex hormone binding globulin (SHBG)) leading to increased total circulating corticosteroids and sex steroids, respectively. Free hormone concentrations may be decreased. Other plasma proteins may be increased (angiotensinogen/renin substrate, alpha-1-antitrypsin, ceruloplasmin).
4. Increased plasma HDL and HDL2cholesterol subfraction concentrations, reduced LDL cholesterol concentration, increased triglycerides levels.
5. Impaired glucose tolerance.
6. Reduced response to metyrapone test.

Drug Interactions (Androgens)

Anticoagulants:C-17 substituted derivatives of testosterone, such as methandrostenolone, have been reported to decrease the anticoagulant requirements of patients receiving oral anticoagulants. Patients receiving oral anticoagulant therapy require close monitoring, especially when androgens are started or stopped.

Oxyphenbutazone: Concurrent administration of oxyphenbutazone and androgens may result in elevated serum levels of oxyphenbutazone.

Insulin:In diabetic patients, the metabolic effects of androgens may decrease blood glucose and insulin requirements.

Drug/Laboratory Test Interferences (Androgens)

Androgens may decrease levels of thyroxine-binding globulin, resulting in decreased T4 serum levels and increased resin uptake of T3 and T4. Free thyroid hormone levels remain unchanged, however, and there is no clinical evidence of thyroid dysfunction.

Carcinogenesis, Mutagenesis, Impairment of Fertility (Estrogens)

Long-term continuous administration of estrogen, with and without progestin, in women with and without a uterus, has shown an increased risk of endometrial cancer, breast cancer, and ovarian cancer. (See BOXED WARNINGS, WARNINGSand PRECAUTIONS.)

Long-term continuous administration of natural and synthetic estrogens in certain animal species increases the frequency of carcinomas of the breast, uterus, cervix, vagina, testis, and liver.

Carcinogenesis (Androgens)

Animal Data:Testosterone has been tested by subcutaneous injection and implantation in mice and rats. The implant induced cervical-uterine tumors in mice, which metastasized in some cases. There is suggestive evidence that injection of testosterone into some strains of female mice increases their susceptibility to hepatoma. Testosterone is also known to increase the number of tumors and decrease the degree of differentiation of chemically induced carcinomas of the liver in rats.

Human Data: There are rare reports of hepatocellular carcinoma in patients receiving long-term therapy with androgens in high doses. Withdrawal of the drugs did not lead to regression of the tumors in all cases.

Geriatric patients treated with androgens may be at increased risk for the development of prostatic hypertrophy and prostatic carcinoma.

Pregnancy (Estrogens)

Esterified Estrogens and Methyltestosterone Tablets and Esterified Estrogens and Methyltestosterone Half-Strength Tablets should not be used during pregnancy. (See CONTRAINDICATIONS.)

Pregnancy (Androgens)

Teratogenic Effects:Pregnancy Category X. (See CONTRAINDICATIONS.)

Nursing Mothers (Estrogens)

Estrogen administration to nursing mothers has been shown to decrease the quantity and quality of the milk. Detectable amounts of estrogens have been identified in the milk of mothers receiving this drug. Caution should be exercised when Esterified Estrogens and Methyltestosterone Tablets Full and Half-Strength Tablets are administered to a nursing woman.

Nursing Mothers (Androgens)

It is not known whether androgens are excreted in human milk. Because many drugs are excreted in human milk and because of the potential for serious adverse reactions in nursing infants from androgens, a decision should be made whether to discontinue nursing or to discontinue the drug, taking into account the importance of the drug to the mother.

Pediatric Use

Esterified Estrogens and Methyltestosterone Tablets Full and Half-Strength Tablets are not indicated for use in children.

Geriatric Use

Clinical studies of Esterified Estrogens and Methyltestosterone Full and Half-Strength Tablets did not include sufficient numbers of subjects aged 65 and over to determine whether they respond differently from younger subjects. Other reported clinical experience has not identified differences in responses between the elderly and younger patients. In general, dose selection for an elderly patient should be cautious, usually starting at the low end of the dosing range, reflecting the greater frequency of decreased hepatic, renal, or cardiac function, and of concomitant disease or other drug therapy.

In the Women's Health Initiative Memory Study, including 4,532 women 65 years of age and older, followed for an average of 4 years, 82% (n = 3,729) were 65 to 74 while 18% (n = 803) were 75 and over. Most women (80%) had no prior hormone therapy use. Women treated with conjugated estrogens plus medroxyprogesterone acetate were reported to have a two-fold increase in the risk of developing probable dementia. Alzheimer's disease was the most common classification of probable dementia in both the conjugated estrogens plus medroxyprogesterone acetate group and the placebo group. Ninety percent of the cases of probable dementia occurred in the 54% of women that were older than 70. (See WARNINGS, Dementia.)

The estrogen alone substudy of the Women's Health Initiative Memory Study has concluded. It is unknown whether these findings apply to estrogen alone.

ADVERSE REACTIONS

See BOXED WARNINGS, WARNINGSand PRECAUTIONS.

Because clinical trials are conducted under widely varying conditions, adverse reaction rates observed in the clinical trials of a drug cannot be directly compared to rates in the clinical trials of another drug and may not reflect the rates observed in practice. The adverse reaction information from clinical trials does, however, provide a basis for identifying the adverse events that appear to be related to drug use and for approximating rates.

Associated with Estrogens

(See WARNINGSregarding induction of neoplasia, adverse effects on the fetus, increased incidence of gallbladder disease, and adverse effects similar to those of oral contraceptives, including thromboembolism). The following additional adverse reactions have been reported with estrogen and/or progestin therapy.

Genitourinary System:Changes in vaginal bleeding pattern and abnormal withdrawal bleeding or flow; breakthrough bleeding; spotting; dysmenorrhea, increase in size of uterine leiomyomata; vaginitis, including vaginal candidiasis; change in amount of cervical secretion; changes in cervical ectropion; ovarian cancer; endometrial hyperplasia; endometrial cancer; cystitis-like syndrome.

Breasts:Tenderness; enlargement; pain, nipple discharge, galactorrhea; fibrocystic breast changes; breast cancer.

Cardiovascular:Deep and superficial venous thrombosis; pulmonary embolism; thrombophlebitis; myocardial infarction; stroke; increase in blood pressure.

Gastrointestinal:Nausea; vomiting; abdominal cramps; bloating; cholestatic jaundice; increased incidence of gallbladder disease; pancreatitis, enlargement of hepatic hemangiomas.

Skin:Chloasma or melasma that may persist when drug is discontinued; erythema multiforme; erythema nodosum; hemorrhagic eruption; loss of scalp hair; hirsutism; pruritus, rash.

Eyes:Retinal vascular thrombosis, steepening of corneal curvature, intolerance to contact lenses.

Central Nervous System:Headache, migraine, dizziness; mental depression; chorea; nervousness; mood disturbances; irritability; exacerbation of epilepsy, dementia.

Miscellaneous:Increase or decrease in weight; reduced carbohydrate tolerance; aggravation of porphyria; edema; arthralgias; leg cramps; changes in libido; urticaria, angioedema, anaphylactoid/anaphylactic reactions; hypocalcemia; exacerbation of asthma; increased triglycerides.

Associated with Methyltestosterone

Endocrine and Urogenital

Female:The most common side effects of androgen therapy are amenorrhea and other menstrual irregularities, inhibition of gonadotropin secretion, and virilization, including deepening of the voice and clitoral enlargement. The latter usually is not reversible after androgens are discontinued. When administered to a pregnant woman, androgens cause virilization of external genitalia of the female fetus.

Skin and Appendages:Hirsutism, male pattern of baldness, and acne.

Fluid and Electrolyte Disturbances:Retention of sodium, chloride, water, potassium, calcium, and inorganic phosphates.

Gastrointestinal:Nausea, cholestatic jaundice, alterations in liver function test, rarely hepatocellular neoplasms, and peliosis hepatis. (See WARNINGS.)

Hematologic:Suppression of clotting factors II, V, VII, and X, bleeding in patients on concomitant anticoagulant therapy, and polycythemia.

Central Nervous System:Increased or decreased libido, headache, anxiety, depression, and generalized paresthesia.

Metabolic:Increased serum cholesterol.

Miscellaneous:Inflammation and pain at the site of intramuscular injection or subcutaneous implantation of testosterone containing pellets, stomatitis with buccal preparations, and rarely anaphylactoid reactions.

DRUG ABUSE AND DEPENDENCE

Methyltestosterone is classified as a schedule III Controlled Substance under the Anabolic Steroids Act of 1990.

OVERDOSAGE

Serious ill effects have not been reported following acute ingestion of large doses of estrogen-containing drug products by young children. Overdosage of estrogen may cause nausea and vomiting, and withdrawal bleeding may occur in females.

There have been no reports of acute overdosage with the androgens.

DOSAGE AND ADMINISTRATION

When estrogen is prescribed for a postmenopausal woman with a uterus, a progestin should also be initiated to reduce the risk of endometrial cancer. A woman without a uterus does not need progestin. Use of estrogen, alone or in combination with a progestin, should be with the lowest effective dose and for the shortest duration consistent with treatment goals and risks for the individual woman. Patients should be reevaluated periodically as clinically appropriate (e.g., 3-month to 6-month intervals) to determine if treatment is still necessary. (See BOXED WARNINGSand WARNINGS.) For women who have a uterus, adequate diagnostic measures, such as endometrial sampling, when indicated, should be undertaken to rule out malignancy in cases of undiagnosed persistent or recurring abnormal vaginal bleeding.

Given cyclically for short-term use only:

For treatment of moderate to severe vasomotor symptoms associated with the menopause in patients not improved by estrogen alone.

The lowest dose that will control symptoms should be chosen and medication should be discontinued as promptly as possible.

Administration should be cyclic (e.g., three weeks on and one week off).

Attempts to discontinue or taper medication should be made at three- to six-month intervals.

Usual Dosage Range:

1 tablet of Esterified Estrogens and Methyltestosterone or 1 to 2 tablets of Esterified Estrogens and Methyltestosterone Half-Strength daily as recommended by the physician.

Treated patients with an intact uterus should be monitored closely for signs of endometrial cancer and appropriate diagnostic measures should be taken to rule out malignancy in the event of persistent or recurring abnormal vaginal bleeding.

HOW SUPPLIED

Esterified Estrogens and Methyltestosterone Tablets (Imprinted “1490”)

- Bottles of 100 tablets: NDC 72162-1747-01

Esterified Estrogens and Methyltestosterone Tablets (dark green, capsule shaped, sugar-coated oral tablets) contain: 1.25 mg of Esterified Estrogens, USP and 2.5 mg of Methyltestosterone, USP.

Keep Esterified Estrogens and Methyltestosterone Tablets and Esterified Estrogens and Methyltestosterone Half-Strength Tablets out of reach of children.

Store at 20° - 25°C (68° - 77°F); excursions permitted to 15° - 30°C (59° - 86°F). [See USP Controlled Room Temperature]

† This product has not obtained FDA pre-market approval applicable for new drugs.

Repackaged/Relabeled by:
Bryant Ranch Prepack, Inc.
Burbank, CA 91504

PATIENT INFORMATION

WHAT YOU SHOULD KNOW ABOUT ESTROGENS

Esterified Estrogens and Methyltestosterone Tablets, 1.25 mg/2.5 mg † and Esterified Estrogens and Methyltestosterone Tablets, 0.625 mg/1.25 mg (Half-Strength) †CIII

Rx Only

Read this PATIENT INFORMATION before you start taking Esterified Estrogens and Methyltestosterone Full and Half-Strength Tablets and read what you get each time you refill Esterified Estrogens and Methyltestosterone Full and Half-Strength Tablets. There may be new information. This information does not take the place of talking to your healthcare provider about your medical condition or your treatment.

BOXED WARNING

WHAT IS THE MOST IMPORTANT INFORMATION I SHOULD KNOW ABOUT ESTERIFIED ESTROGENS AND METHYLTESTOSTERONE TABLETS AND ESTERIFIED ESTROGENS AND METHYLTESTOSTERONE HALF-STRENGTH TABLETS (A COMBINATION OF ESTROGEN AND ANDROGEN HORMONES)?

- Estrogens increase the chances of getting cancer of the uterus.
  Report any unusual vaginal bleeding right away while you are taking estrogens .Vaginal bleeding after menopause may be a warning sign of cancer of the uterus (womb). Your healthcare provider should check any unusual vaginal bleeding to find out the cause.
- Do not use estrogens with or without progestins to prevent heart disease, heart attacks, or strokes.
  Using estrogens with or without progestins may increase your chances of getting heart attacks, strokes, breast cancer, and blood clots. Using estrogens with progestins may increase your risk of dementia. You and your healthcare provider should talk regularly about whether you still need treatment with Esterified Estrogens and Methyltestosterone Full and Half-Strength Tablets.

What are Esterified Estrogens and Methyltestosterone Tablets and Esterified Estrogens and Methyltestosterone Half-Strength Tablets?

Esterified Estrogens and Methyltestosterone Full and Half-Strength Tablets are medicines that contain estrogen and androgen hormones.

What are Esterified Estrogens and Methyltestosterone Tablets and Esterified Estrogens and Methyltestosterone Half-Strength Tablets used for?

Esterified Estrogens and Methyltestosterone Full and Half-Strength Tablets are used after menopause to:

- reduce moderate to severe hot flashes.Estrogens are hormones made by a woman's ovaries. The ovaries normally stop making estrogens when a woman is between 45 to 55 years old. This drop in body estrogen levels causes the "change of life" or menopause (the end of monthly menstrual periods). Sometimes, both ovaries are removed during an operation before natural menopause takes place. The sudden drop in estrogen levels causes "surgical menopause."
  When the estrogen levels begin dropping, some women develop very uncomfortable symptoms, such as feelings of warmth in the face, neck, and chest, or sudden strong feelings of heat and sweating ("hot flashes" or "hot flushes"). In some women, the symptoms are mild, and they will not need estrogens. In other women, symptoms can be more severe. You and your healthcare provider should talk regularly about whether you still need treatment with Esterified Estrogens and Methyltestosterone Full and Half-Strength Tablets.
- treat moderate to severe dryness, itching, and burning in and around the vagina.You and your healthcare provider should talk regularly about whether you still need treatment with Esterified Estrogens and Methyltestosterone Full and Half-Strength Tablets to control these problems. If you use Esterified Estrogens and Methyltestosterone Full and Half-Strength Tablets only to treat your dryness, itching, and burning in and around your vagina, talk with your healthcare provider about whether a topical vaginal product would be better for you.

Who should not take Esterified Estrogens and Methyltestosterone Tablets and Esterified Estrogens and Methyltestosterone Half-Strength Tablets?

Do not start taking Esterified Estrogens and Methyltestosterone Full and Half-Strength Tablets if you:

- have unusual vaginal bleeding.
- currently have or have had certain cancers.Estrogens may increase the chances of getting certain types of cancers, including cancer of the breast or uterus. If you have or had cancer, talk with your healthcare provider about whether you should take Esterified Estrogens and Methyltestosterone Full and Half-Strength Tablets.
- had a stroke or heart attack in the past year.
- currently have or have had blood clots.
- currently have or have had liver problems.
- are allergic to Esterified Estrogens and Methyltestosterone Tablets and Esterified Estrogens and Methyltestosterone Half-Strength Tablets or any of their ingredients.See the end of this leaflet for a list of ingredients in Esterified Estrogens and Methyltestosterone Full and Half-Strength Tablets.
- think you may be pregnant.

Tell your healthcare provider:

- if you are breastfeeding.The hormones in Esterified Estrogens and Methyltestosterone Full and Half-Strength Tablets can pass into your milk.
- about all of your medical problems.Your healthcare provider may need to check you more carefully if you have certain conditions, such as asthma (wheezing), epilepsy (seizures), migraine, endometriosis, lupus, problems with your heart, liver, thyroid, kidneys, or have high calcium levels in your blood.
- about all the medicines you take. This includes prescription and nonprescription medicines, vitamins, and herbal supplements. Some medicines may affect how Esterified Estrogens and Methyltestosterone Full and Half-Strength Tablets work. Esterified Estrogens and Methyltestosterone Full and Half-Strength Tablets may also affect how your other medicines work.
- if you are going to have surgery or will be on bed rest.You may need to stop taking estrogens.

How should I take Esterified Estrogens and Methyltestosterone Tablets and Esterified Estrogens and Methyltestosterone Half-Strength Tablets?

Estrogens should be used at the lowest dose possible for your treatment only as long as needed. The lowest effective dose of Esterified Estrogens and Methyltestosterone Full and Half-Strength Tablets has not been determined. You and your healthcare provider should talk regularly (for example, every 3 to 6 months) about the dose you are taking and whether you still need treatment with Esterified Estrogens and Methyltestosterone Full and Half-Strength Tablets.

What are the possible side effects of estrogens?

Less common but serious side effects include:

- Breast cancer
- Cancer of the uterus
- Stroke
- Heart attack
- Blood clots
- Dementia
- Gallbladder disease
- Ovarian cancer

These are some of the warning signs of serious side effects:

- Breast lumps
- Unusual vaginal bleeding
- Dizziness and faintness
- Changes in speech
- Severe headaches
- Chest pain
- Shortness of breath
- Pains in your legs
- Changes in vision
- Vomiting

Call your healthcare provider right away if you get any of these warning signs, or any other unusual symptom that concerns you.

Common side effects include:

- Headache
- Breast pain
- Irregular vaginal bleeding or spotting
- Stomach/abdominal cramps, bloating
- Nausea and vomiting
- Hair loss

Other side effects include:

- High blood pressure
- Liver problems
- High blood sugar
- Fluid retention
- Enlargement of benign tumors of the uterus ("fibroids")
- Vaginal yeast infection

These are not all the possible side effects of Esterified Estrogens and Methyltestosterone Full and Half-Strength Tablets. For more information, ask your healthcare provider or pharmacist.

What can I do to lower my chance of a serious side effect with Esterified Estrogens and Methyltestosterone Tablets and Esterified Estrogens and Methyltestosterone Half-Strength Tablets?

- Talk with your healthcare provider regularly about whether you should continue taking Esterified Estrogens and Methyltestosterone Full and Half-Strength Tablets.
- If you have a uterus, talk to your healthcare provider about whether the addition of a progestin is right for you.
- See your healthcare provider right away if you get vaginal bleeding while taking Esterified Estrogens and Methyltestosterone Full and Half-Strength Tablets.
- Have a breast exam and mammogram (breast X-ray) every year unless your healthcare provider tells you something else. If members of your family have had breast cancer or if you have ever had breast lumps or an abnormal mammogram, you may need to have breast exams more often.
- If you have high blood pressure, high cholesterol (fat in the blood), diabetes, are overweight, or if you use tobacco, you may have higher chances for getting heart disease. Ask your healthcare provider for ways to lower your chances for getting heart disease.

General information about safe and effective use of Esterified Estrogens and Methyltestosterone Tablets and Esterified Estrogens and Methyltestosterone Half-Strength Tablets

Medicines are sometimes prescribed for conditions that are not mentioned in patient information leaflets. Do not take Esterified Estrogens and Methyltestosterone Full and Half-Strength Tablets for conditions for which it was not prescribed. Do not give Esterified Estrogens and Methyltestosterone Full and Half-Strength Tablets to other people, even if they have the same symptoms you have. It may harm them.

Keep Esterified Estrogens and Methyltestosterone Tablets and Esterified Estrogens and Methyltestosterone Half-Strength Tablets out of the reach of children.

This leaflet provides a summary of the most important information about Esterified Estrogens and Methyltestosterone Full and Half-Strength Tablets. If you would like more information, talk with your healthcare provider or pharmacist. You can ask for information about Esterified Estrogens and Methyltestosterone Full and Half-Strength Tablets that is written for health professionals. You can get more information by calling the toll free number 1-800-308-6755.

What are the ingredients in Esterified Estrogens and Methyltestosterone Tablets and Esterified Estrogens and Methyltestosterone Half-Strength Tablets?

Esterified Estrogens and Methyltestosterone Half-Strength Tablets is a combination of Esterified Estrogens and Methyltestosterone. Each light green, capsule shaped, sugar-coated tablet imprinted with “1507" contains the following active ingredients: 0.625 mg of Esterified Estrogens, USP and 1.25 mg of Methyltestosterone, USP.

Esterified Estrogens and Methyltestosterone Tablets is a combination of Esterified Estrogens and Methyltestosterone. Each dark green, capsule shaped, sugar-coated tablet imprinted with “1490” contains the following active ingredients: 1.25 mg of Esterified Estrogens, USP and 2.5 mg of Methyltestosterone, USP.

Esterified Estrogens and Methyltestosterone Full and Half-Strength Tablets contain the following inactive ingredients: acacia, calcium carbonate, carnauba wax, citric acid, colloidal silicon dioxide, di-acetylated monoglycerides, gelatin, lactose, magnesium stearate, methylparaben, microcrystalline cellulose, pharmaceutical glaze, povidone, propylene glycol, propylparaben, shellac glaze, sodium benzoate, sodium bicarbonate, sorbic acid, starch, sucrose, talc, titanium dioxide, tromethamol, FD&C Blue No. 1 Aluminum Lake, and D&C Yellow No. 10 Aluminum Lake.

Esterified Estrogens and Methyltestosterone Tablets also contain: FD&C Yellow No. 6 Aluminum Lake.

Esterified Estrogens and Methyltestosterone Half-Strength Tablets also contain: FD&C Blue No. 2 Aluminum Lake and Iron Oxide Black.

Store at 20° - 25°C (68° - 77°F); excursions permitted to 15° - 30°C (59° - 86°F). [See USP Controlled Room Temperature]

†This product has not obtained FDA pre-market approval applicable for new drugs.

DEA Order Form Required

Manufactured by:
ANI Pharmaceuticals, Inc.
Baudette, MN 56623

10752 Rev 07/24

PACKAGE LABEL

Esterified Estrogens and Methyltestosterone 1.25mg/2.5mg Tablets (CIII)